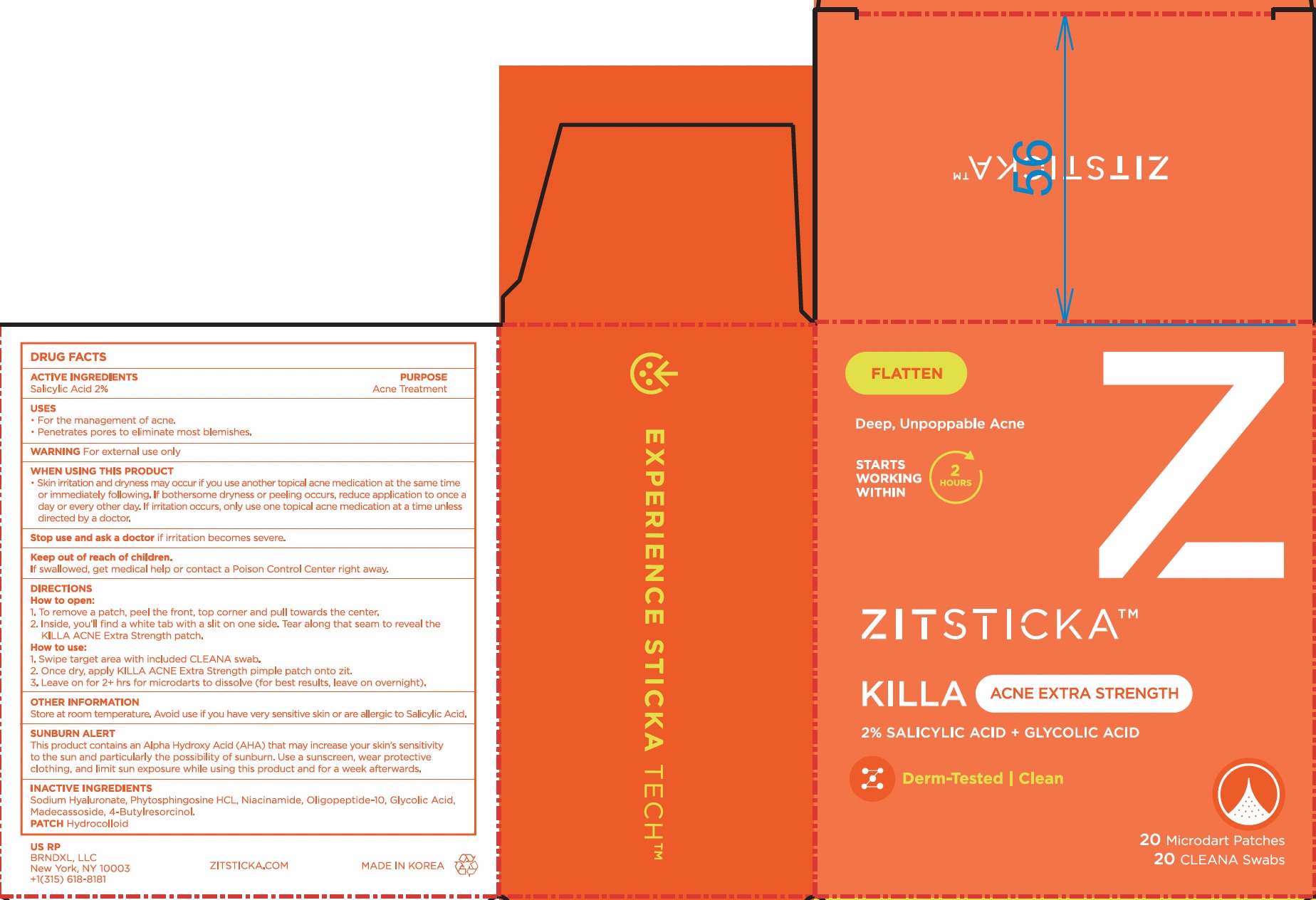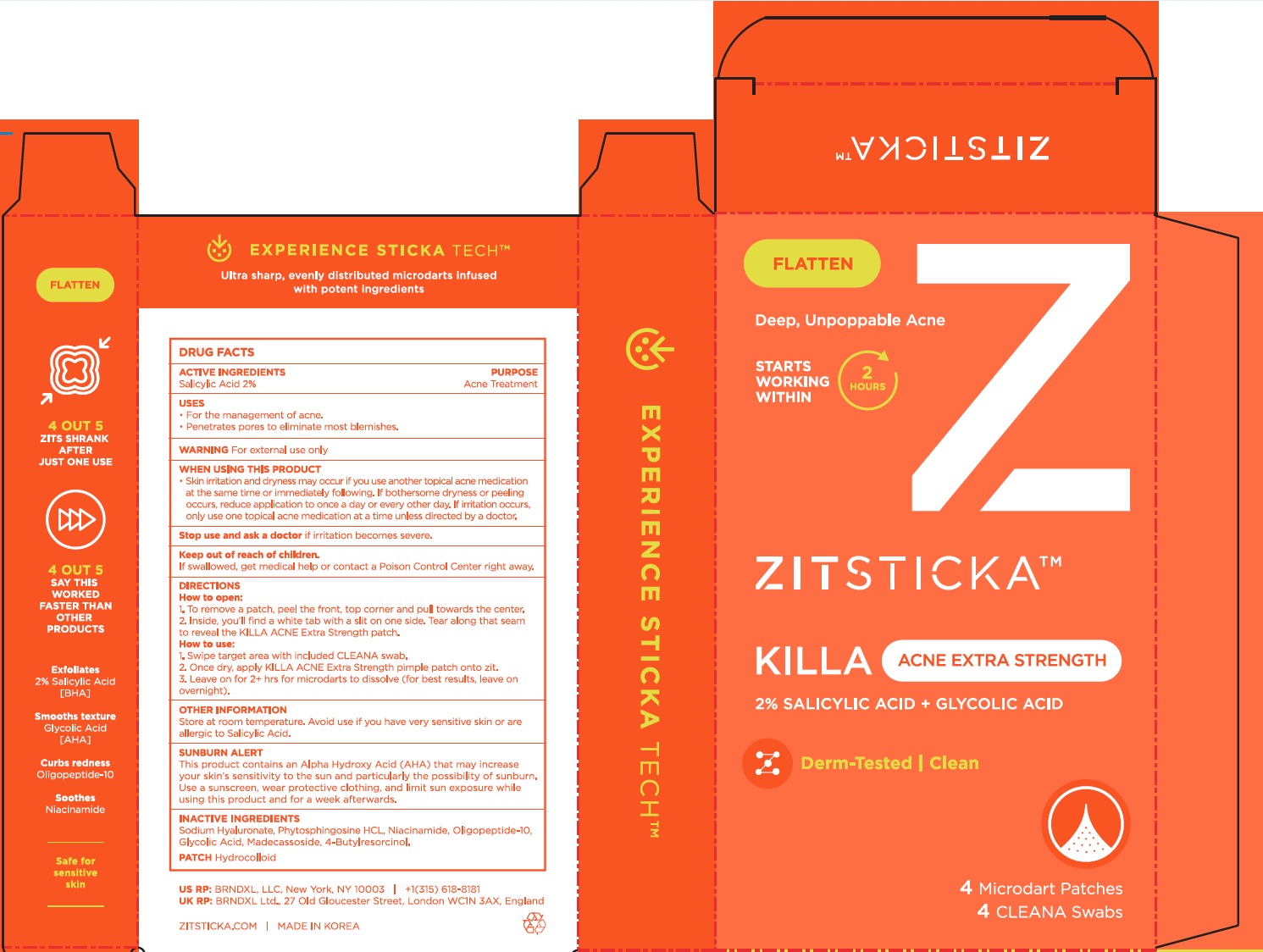 DRUG LABEL: Zitsticka Killa Acne Extra Strength
NDC: 83742-444 | Form: PATCH
Manufacturer: Brndxl LLC
Category: otc | Type: HUMAN OTC DRUG LABEL
Date: 20251218

ACTIVE INGREDIENTS: SALICYLIC ACID 2 g/100 g
INACTIVE INGREDIENTS: GLYCOLIC ACID; NIACINAMIDE; MADECASSOSIDE; SODIUM HYALURONATE; 4-BUTYLRESORCINOL; OLIGOPEPTIDE-10; PHYTOSPHINGOSINE HYDROCHLORIDE

INACTIVE INGREDIENT

Sodium Hyaluonate, Phytosphingosine HCL, Niacinamide, Oligopeptide-10, Glycolic Acid, Madecassoside, 4-Butyl-Resorcinol

WARNINGS

For external use only

ACTIVE INGREDIENT

Salicylic Acid 2%

Keep out of reach of children. If swallowed, get medical help or contact a Poison Control Center right away.

PURPOSE

Acne Treatment

INDICATIONS AND USAGE

- For the management of acne.
- Penetrates pores to eliminate most blemishes.

DOSAGE AND ADMINISTRATION

1. Swipe target area with included CLEANA swab.
2. Once dry, apply KILLA ACNE Extra Strength pimple patch onto zit.
3. Leave on for 2+ hrs for microdarts to dissolve (for best results, leave on overnight).